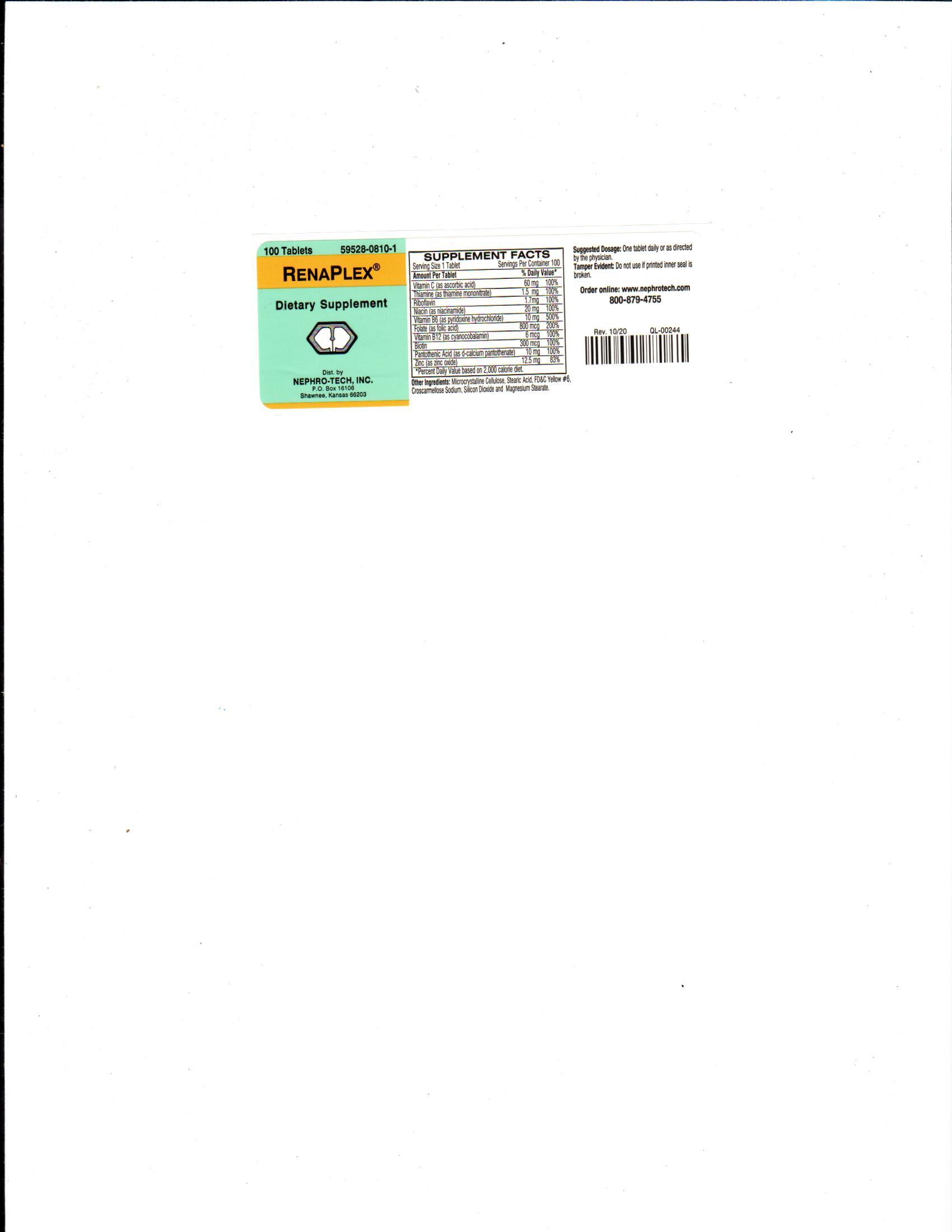 DRUG LABEL: RenaPlex
NDC: 59528-0810 | Form: TABLET, COATED
Manufacturer: Nephro-Tech, Inc.
Category: other | Type: Dietary Supplement
Date: 20210715

ACTIVE INGREDIENTS: ASCORBIC ACID 60 mg/1 1; THIAMINE 1500 ug/1 1; RIBOFLAVIN 1700 ug/1 1; NIACINAMIDE 20 mg/1 1; PYRIDOXINE HYDROCHLORIDE 10 mg/1 1; FOLIC ACID 800 ug/1 1; CYANOCOBALAMIN 6 ug/1 1; BIOTIN 300 ug/1 1; PANTOTHENIC ACID 10 mg/1 1; ZINC OXIDE 12.5 mg/1 1

RenaPlex (ascorbic acid, thiamin mononitrate, riboflavin, niacamide, pyridoxine hydrochloride, folic acid, cyanocobalamin, biotin, pantothenic acid and zinc)

Suggested Dosage

One tablet daily or as directed by the physician.

Package Label/Principal Display Panel

59528-0810-1

RenaPlex

Dietary Supplement

100 Tablets

Dietary Supplement

Minerals and vitamins